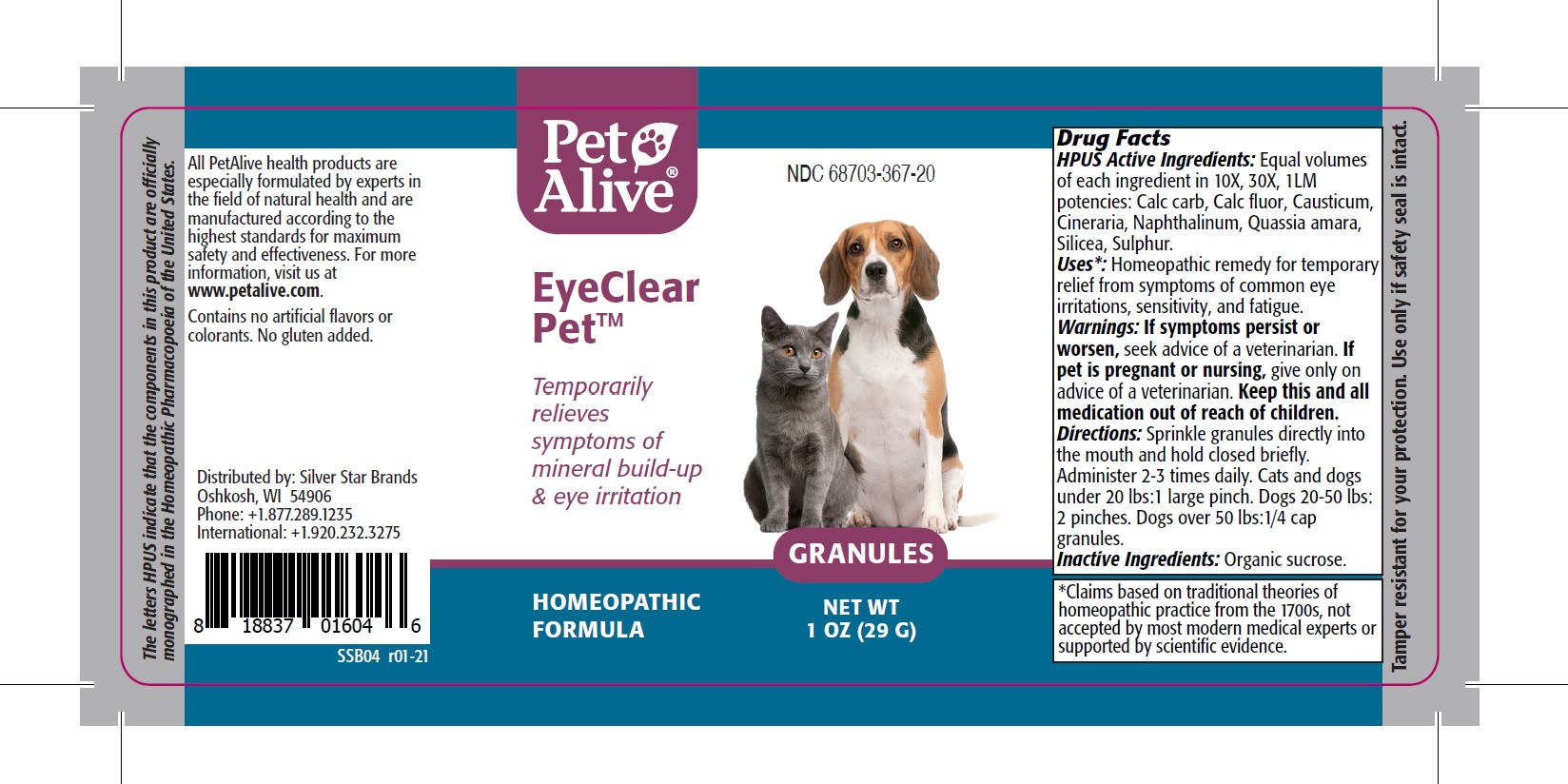 DRUG LABEL: PetAlive EyeClear Pet
NDC: 68703-367 | Form: GRANULE
Manufacturer: SILVER STAR BRANDS
Category: homeopathic | Type: OTC ANIMAL DRUG LABEL
Date: 20251216

ACTIVE INGREDIENTS: OYSTER SHELL CALCIUM CARBONATE, CRUDE 10 [hp_X]/26.67 mg; CALCIUM FLUORIDE 10 [hp_X]/26.67 mg; CAUSTICUM 10 [hp_X]/26.67 mg; JACOBAEA MARITIMA 10 [hp_X]/26.67 mg; NAPHTHALENE 10 [hp_X]/26.67 mg; QUASSIA AMARA WOOD 10 [hp_X]/26.67 mg; SILICON DIOXIDE 10 [hp_X]/26.67 mg; SULFUR 10 [hp_X]/26.67 mg

PetAlive EyeClear Pet

PURPOSE

Temporarily relieves symptoms of mineral build-up AND eye irritation

HPUS Active Ingredients:

Calc carb 10X, 30X, 1LM
Calc fluor 10X, 30X, 1LM
Causticum 10X, 30X, 1LM
Cineraria 10X, 30X, 1LM
Naphthalinum 10X, 30X, 1LM
Quassia amara 10X, 30X, 1LM
Silicea 10X, 30X, 1LM
Sulphur 10X, 30X, 1LM

INDICATIONS AND USAGE

Uses: Homeopathic remedy for temporary relief from symptoms of common eye irritations, sensitivity, and fatigue.

WARNINGS

Warnings: If symptoms persist or worsen, seek advice of a veterianrian

PREGNANCY OR BREAST FEEDING

If pregnant or nursing give only on advice of a veterinarian

KEEP OUT OF REACH OF CHILDREN

Keep this and all medication out of reach of children

DOSAGE AND ADMINISTRATION

Directions: Sprinkle granules directly into the mouth and hold closed briefly. Administer 2-3 times daily. Cats and dogs under 20 lbs:1 large pinch. Dogs 20-50 lbs: 2 pinches. Dogs over 50 lbs:1/4 cap granules.

Inactive Ingredients: Organic sucrose

INFORMATION FOR OWNERS/CAREGIVERS

The letters HPUS indicate that the components in this product are officially monographed in the Homeopathic Pharmacopoeia of the United States.

All PetAlive health products are especially formulated by experts in the field of natural health and are manufactured according to the highest standards for maximum safety and effectiveness. For more information, visit us at www.petalive.com.

Contains no artificial flavors or colorants. No gluten added.

Distributed by: Silver Star Brands
Oshkosh, WI 54906
Phone: +1.877.289.1235
International: +1.920.232.3275

STORAGE AND HANDLING

Tamper resistant for your protection. Use only if safety seal is intact.